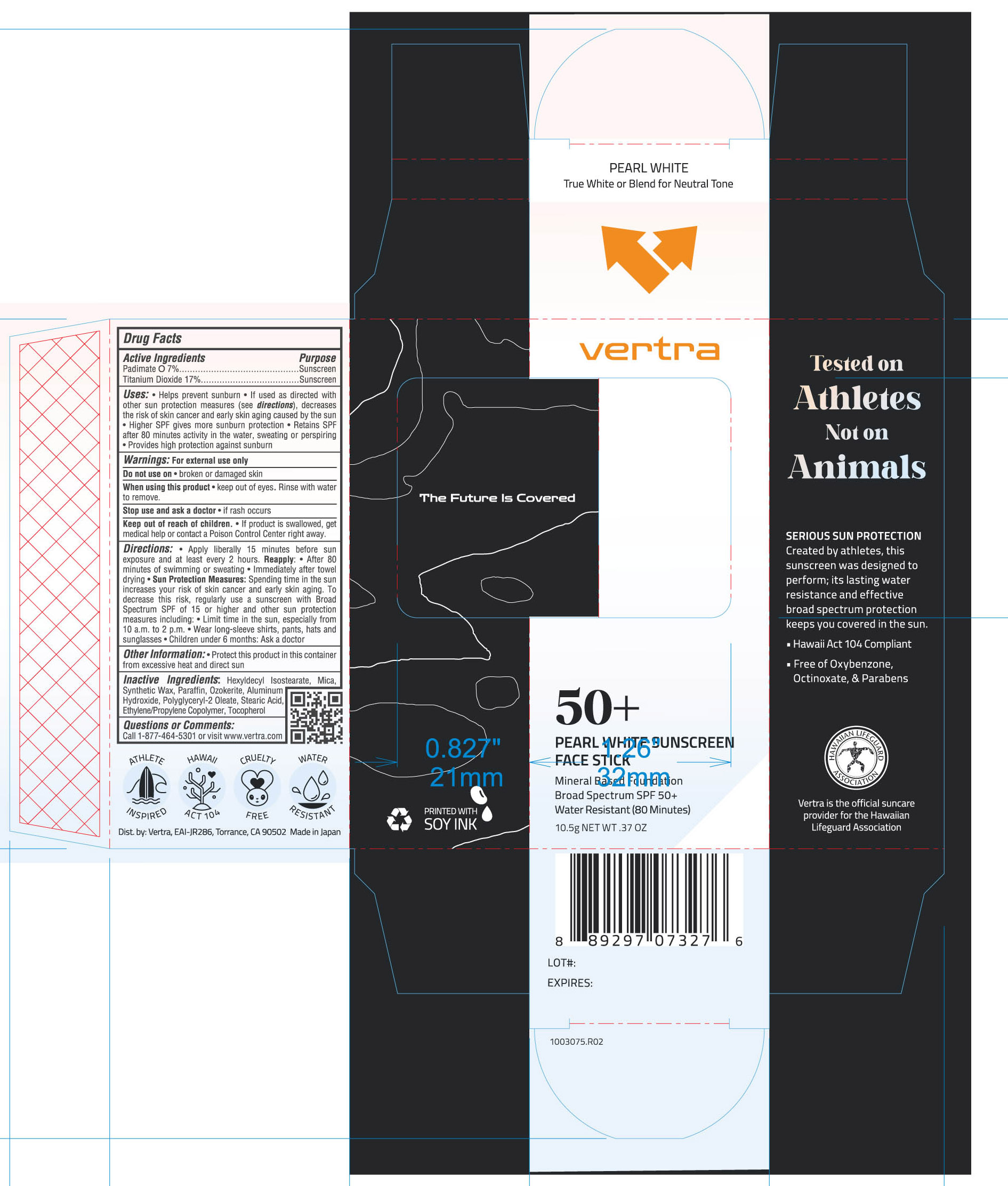 DRUG LABEL: Vertra Pearl White Face Stick SPF 50
NDC: 66990-1019 | Form: STICK
Manufacturer: Toshiki Pigment Co., ltd.
Category: otc | Type: HUMAN OTC DRUG LABEL
Date: 20251104

ACTIVE INGREDIENTS: PADIMATE O 7 g/100 g; TITANIUM DIOXIDE 17 g/100 g
INACTIVE INGREDIENTS: TOCOPHEROL; PARAFFIN; HEXYLDECYL ISOSTEARATE; SYNTHETIC WAX (1200 MW); POLYGLYCERYL-2 OLEATE; ALUMINUM HYDROXIDE; MICA; CERESIN; STEARIC ACID

Vertra Pearl White Face Stick SPF 50 +

Active Ingredients Purpose

PADIMATE O 7% Sunscreen

TITANIUM DIOXIDE 17% Sunscreen

Uses

- Helps prevent sunburn
- If used as directed with other sun protection (see directions), decreases the risk of skin cancer and early skin aging caused by the sun.
- Higher SPF gives more sunburn protection
- Retains SPF after 80 minutes activity in the water, sweating, or perspiring.
- Provides high protection against sunburn

Keep out of reach of children:

- If product is swallowed get medical help or contact a Poison Control Center right away

Stop use and ask a doctor if:

Rash or irritation develops and lasts

Warnings

Do not use:

- On damaged or broken skin

When using this product:

- keep out of eyes. Rinse with water to remove
- For external use only

Directions

- Apply liberally and generously 15 minutes before sun exposure and at least every 2 hours
- Children under 6 months of age: ask a doctor.
- Sun Protection Measures Spending time in the sun increases your risk of skin cancer and early skin aging. To decrease this risk, regularly use a sunscreen with a Broad-Spectrum SPF value of 15 or higher and other sun protection measures including:
- limit your time in the sun, especially from 10 a.m. – 2 p.m.
- wear long-sleeved shirts, pants, hats, and sunglasses
- Reapply:
- After 80 minutes of swimming or sweating
- Immediately after towel drying
- at least every 2 hours

Inactive Ingredients

Hexyldecyl Isostearate, Mica, Synthetic Wax, Paraffin, Ozokerite, Polyglyceryl-2 Oleate, Aluminum Hydroxide, Stearic Acid, Ethylene/Propylene Copolymer, Tocopherol, Fragrance

PACKAGE LABEL

vertra

50 +

Pearl White Face Stick

Mineral Based Foundation

Broad Spectrum SPF 50+

Water Resistant (80 Minutes)

10.5g NET WT 0.37 OZ